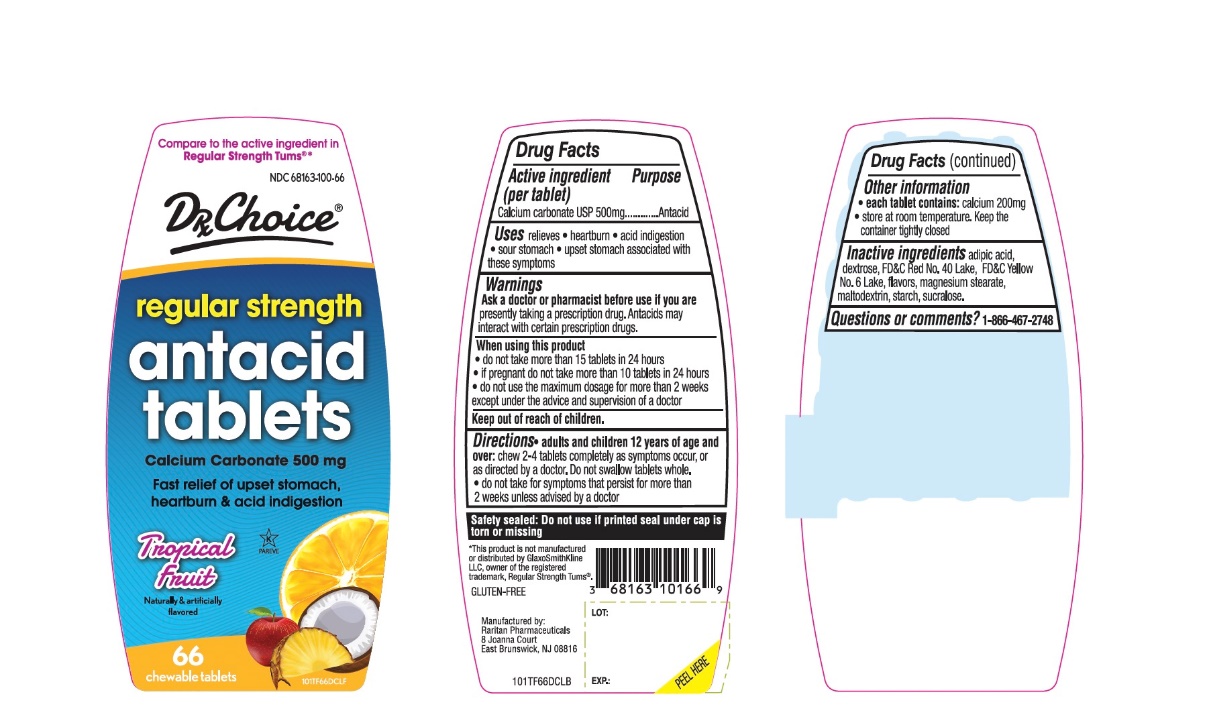 DRUG LABEL: Regular Strength

NDC: 68163-100 | Form: TABLET, CHEWABLE
Manufacturer: RARITAN PHARMACEUTICALS INC
Category: otc | Type: HUMAN OTC DRUG LABEL
Date: 20250926

ACTIVE INGREDIENTS: CALCIUM CARBONATE 500 mg/1 1
INACTIVE INGREDIENTS: ADIPIC ACID; DEXTROSE, UNSPECIFIED FORM; FD&C RED NO. 40; FD&C YELLOW NO. 6; MAGNESIUM STEARATE; MALTODEXTRIN; STARCH, CORN; SUCRALOSE

DRx CHOICE Regular Strength Antacid Tablets

Active ingredient (per tablet)

Calcium Carbonate USP 500 mg

Purpose

Antacid

Uses

relieves:

- heartburn
- acid indigestion,
- sour stomach
- upset stomach associated with these symptoms

Warnings

Ask a doctor before use if youare taking prescription drugs. Antacids may interact with certain prescription drugs .

When using this product

- do not take more than 15 tablets in 24 hours
- If pregnant do not take more than 10 tablets in 24 hours
- do not use the maximum dosage for more than 2 weeks except under the advice and supervision of a doctor

Keep out of reach of children.In case of overdose, get medical help or contact a Poison Control Center right away at 1-800-222-1222.

Directions

- adults and children 12 years of age and over:chew 2-4 tablets completely as symptoms occur or as directed by a doctor. Do not swallow tablets whole
- do not take for symptoms that persist for more than 2 weeks unless advised by a doctor.

Other information

- each tablet contains:elemental calcium 200 mg
- store at room temperature. Keep the container tightly closed

Inactive Ingredients

adipic acid, dextrose, FD&C Red No. 40, FD & C Yellow No. 6, flavor, magnesium stearate, maltodextrin, starch, sucralose.

Questions or comments

1-866-467-2748

Principal Display Panel

DRx CHOICE®

NDC# 68163-100-66

*Compare to the active ingredient in Regular Strength Tums®

REGULAR STRENGTH

Antacid Tablets

Calcium Carbonate 500 mg

Fast Relief of Upset Stomach, Heartburn and Acid Indigestion

Tropical Fruit

Naturally and Artificially Flavored

66 Chewable Tablets

GLUTEN-FREE

Manufactured by:

Raritan Pharmaceuticals

8 Joanna Court

East Brunswick, NJ 08816

This product is not manufactured or distributed by GlaxoSmithKline LLC, owner of the registered trademark, Regular Strength Tums®